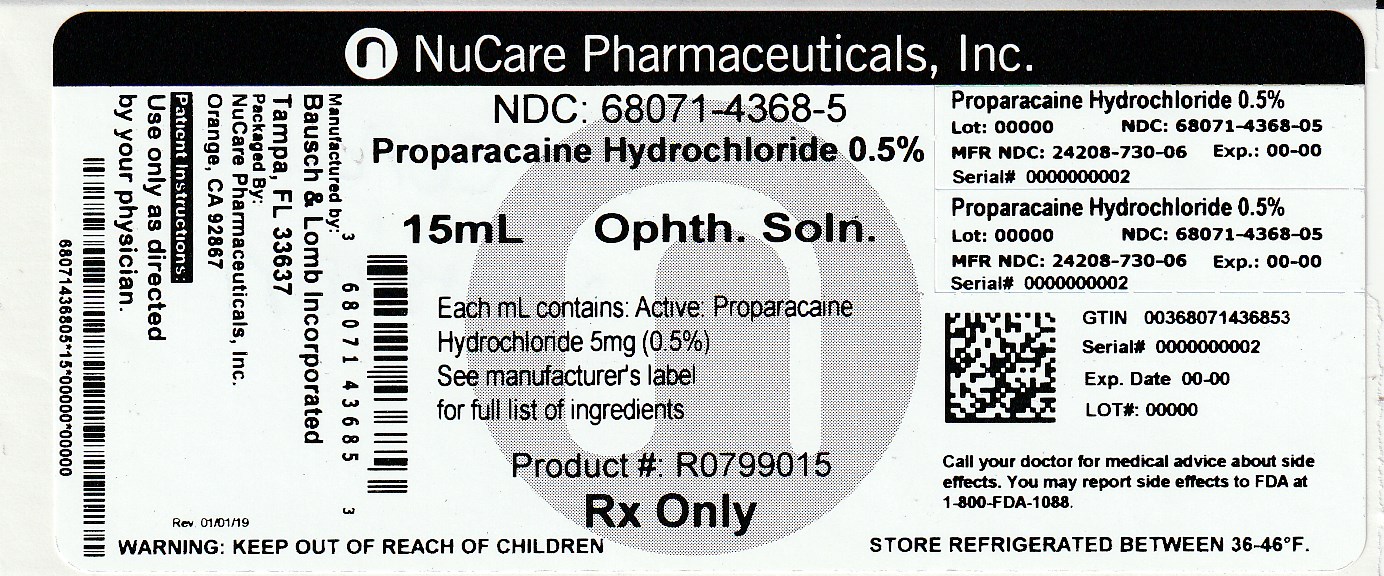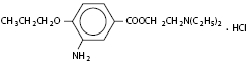 DRUG LABEL: Proparacaine Hydrochloride
NDC: 68071-4368 | Form: SOLUTION/ DROPS
Manufacturer: NuCare Pharmaceuticals,Inc.
Category: prescription | Type: HUMAN PRESCRIPTION DRUG LABEL
Date: 20240607

ACTIVE INGREDIENTS: PROPARACAINE HYDROCHLORIDE 5 mg/1 mL
INACTIVE INGREDIENTS: BENZALKONIUM CHLORIDE; GLYCERIN; HYDROCHLORIC ACID; WATER; SODIUM HYDROXIDE

Proparacaine Hydrochloride Ophthalmic Solution, USP 0.5%
(Sterile)

Rx only

DESCRIPTION

Proparacaine Hydrochloride Ophthalmic Solution, USP 0.5% is a topical local anesthetic for ophthalmic use. The active ingredient is represented by the structural formula:

Established name:

Proparacaine Hydrochloride

Chemical name:
Benzoic acid, 3-amino-4-propoxy-,2-(diethylamino) ethyl ester, monohydrochloride

Molecular weight: 330.85

Each mL contains:

Active: proparacaine hydrochloride 5 mg (0.5%). Inactives: glycerin and purified water. The pH may be adjusted with hydrochloric acid and/or sodium hydroxide. Preservative: benzalkonium chloride (0.01%).

CLINICAL PHARMACOLOGY

Proparacaine hydrochloride ophthalmic solution is a rapidly-acting topical anesthetic, with induced anesthesia lasting approximately 10-20 minutes.

INDICATIONS AND USAGE

Proparacaine hydrochloride ophthalmic solution is indicated for procedures in which a topical ophthalmic anesthetic is indicated; corneal anesthesia of short duration, e.g. tonometry, gonioscopy, removal of corneal foreign bodies and for short corneal and conjunctival procedures.

CONTRAINDICATIONS

Proparacaine hydrochloride ophthalmic solution is contraindicated in patients with known hypersensitivity to any of the ingredients of this preparation.

WARNINGS

NOT FOR INJECTION INTO THE EYE - FOR TOPICAL OPHTHALMIC USE ONLY

Prolonged use of a topical ocular anesthetic is not recommended. It may produce permanent corneal opacification with accompanying visual loss.

PRECAUTIONS

Carcinogenesis, Mutagenesis, Impairment of Fertility

Long-term studies in animals have not been performed to evaluate carcinogenic potential, mutagenicity or possible impairment of fertility in males or females.

Pregnancy

Pregnancy Category C Animal reproduction studies have not been conducted with Proparacaine Hydrochloride Ophthalmic Solution, USP 0.5%. It is also not known whether proparacaine hydrochloride can cause fetal harm when administered to a pregnant woman or can affect reproduction capacity. Proparacaine hydrochloride should be administered to a pregnant woman only if clearly needed.

Nursing Mothers

It is not known whether this drug is excreted in human milk. Because many drugs are excreted in human milk, caution should be exercised when proparacaine hydrochloride is administered to a nursing woman.

Pediatric Use

Safety and effectiveness of proparacaine hydrochloride ophthalmic solution in pediatric patients have been established. Use of proparacaine hydrochloride is supported by evidence from adequate and well-controlled studies in adults and children over the age of twelve, and safety information in neonates and other pediatric patients.

Geriatric Use

No overall clinical differences in safety of effectiveness have been observed between the elderly and other adult patients.

ADVERSE REACTIONS

Occasional temporary stinging, burning and conjunctival redness may occur with the use of proparacaine. A rare, severe, immediate-type, apparently hyperallergic corneal reaction characterized by acute, intense and diffuse epithelial keratitis, a gray, ground glass appearance, sloughing of large areas of necrotic epithelium, corneal filaments and sometimes iritis with descemetitis has been reported.

Allergic contact dermatitis from proparacaine with drying and fissuring of the fingertips has been reported.

To report SUSPECTED ADVERSE REACTIONS, contact Bausch + Lomb, a division of Valeant Pharmaceuticals North America LLC, at 1-800-321-4576 or FDA at 1-800-FDA-1088 or www.fda.gov/medwatch.

DOSAGE AND ADMINISTRATION

Usual dosage: Removal of foreign bodies and sutures, and for tonometry: 1 to 2 drops (in single instillations) in each eye before operating.

Short corneal and conjunctival procedures: 1 drop in each eye every 5 to 10 minutes for 5 to 7 doses.

NOTE: Proparacaine Hydrochloride Ophthalmic Solution, USP 0.5% should be clear, colorless to faint yellow color. If the solution becomes darker, discard the solution.

FOR TOPICAL OPHTHALMIC USE ONLY

HOW SUPPLIED

Proparacaine Hydrochloride Ophthalmic Solution, USP 0.5% is supplied in a plastic bottle with a controlled drop tip and a white polypropylene cap in the following size:

NDC 68071-4368-5 bottles of 15mL

Storage

Refrigerate at 2°-8°C (36°- 46°F). Protect from light. Keep tightly closed.

DO NOT USE IF IMPRINTED NECKBAND IS NOT INTACT.

KEEP OUT OF REACH OF CHILDREN.
Revised: July 2016

Bausch + Lomb, a division of Valeant Pharmaceuticals North America LLC, Bridgewater, NJ 08807 USA
©Bausch & Lomb Incorporated

9114403 (Folded)
9114503 (Flat)